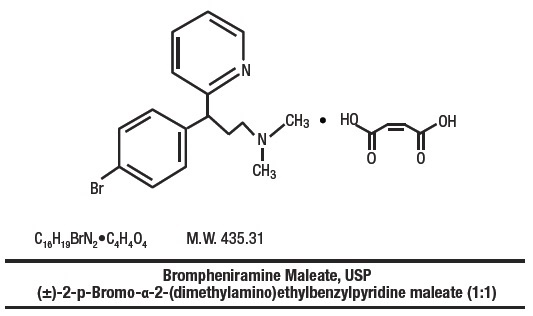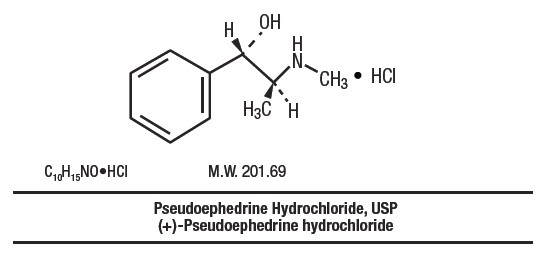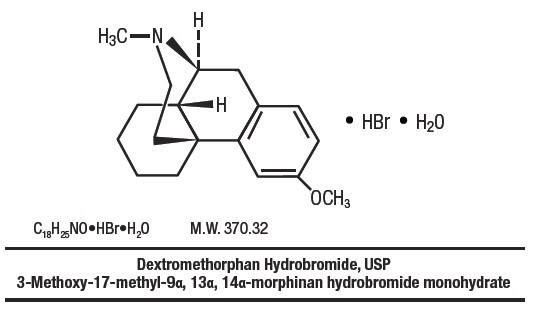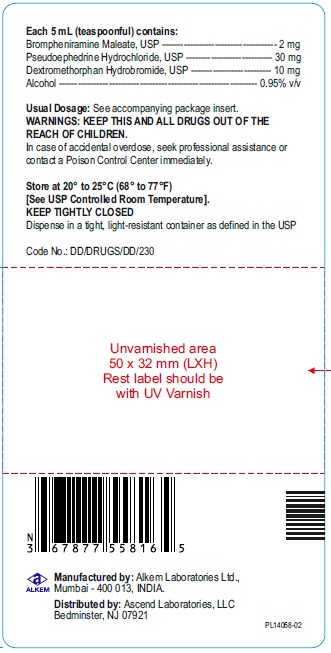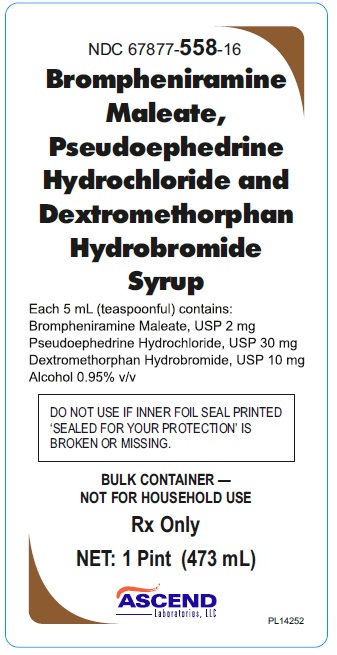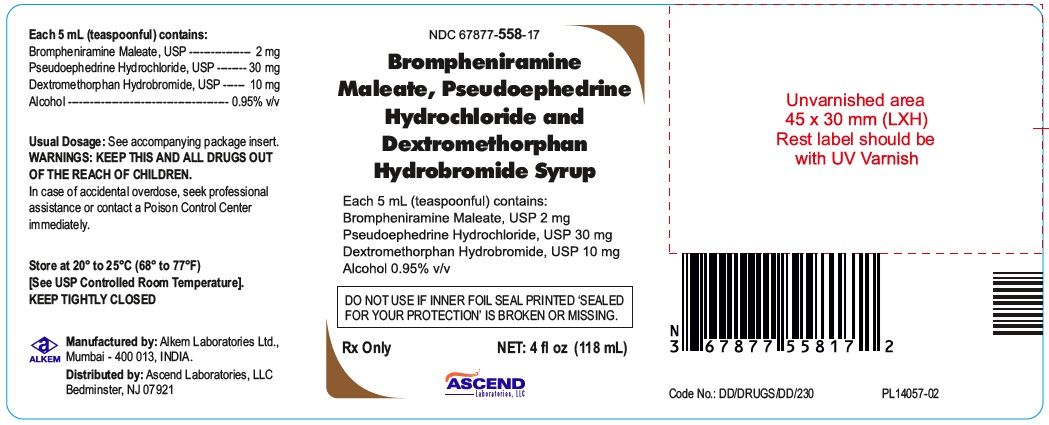 DRUG LABEL: Brompheniramine, Pseudoephedrine, Dextromethorphan
NDC: 67877-558 | Form: SYRUP
Manufacturer: Ascend Laboratories, LLC
Category: prescription | Type: Human Prescription Drug Label
Date: 20260102

ACTIVE INGREDIENTS: BROMPHENIRAMINE MALEATE 2 mg/5 mL; PSEUDOEPHEDRINE HYDROCHLORIDE 30 mg/5 mL; DEXTROMETHORPHAN HYDROBROMIDE 10 mg/5 mL
INACTIVE INGREDIENTS: ALCOHOL; GLYCERIN; SUCROSE; ANHYDROUS CITRIC ACID; FD&C RED NO. 40; METHYLPARABEN; SODIUM BENZOATE; PROPYLENE GLYCOL; SODIUM CITRATE, UNSPECIFIED FORM; WATER

Brompheniramine Maleate, Pseudoephedrine Hydrochloride and Dextromethorphan Hydrobromide Syrup
(Brompheniramine Maleate 2 mg, Pseudoephedrine Hydrochloride 30 mg, and Dextromethorphan Hydrobromide 10 mg)
Rx only

DESCRIPTION

Brompheniramine maleate, pseudoephedrine hydrochloride and dextromethorphan hydrobromide syrup is a clear, light pink syrup with a butterscotch flavor.
Each 5 mL (1 teaspoonful) contains:
Brompheniramine Maleate, USP ----------------- 2 mg
Pseudoephedrine Hydrochloride, USP -------- 30 mg
Dextromethorphan Hydrobromide, USP ------ 10 mg
Alcohol ------------------------------------------- 0.95% v/v
In a palatable, aromatic vehicle.
Inactive Ingredients: dehydrated ethanol, glycerin, sucrose, citric acid anhydrous, spectracol dual FD&C Red No 40, artificial butterscotch flavour, methylparaben, sodium benzoate, propylene glycol, sodium citrate anhydrous and purified water. It may contain 10% sodium citrate solution for pH adjustment. The pH range is between 3.0 and 6.0.

Antihistamine/Nasal Decongestant/Antitussive syrup for oral administration.

CLINICAL PHARMACOLOGY

Brompheniramine maleate is a histamine antagonist, specifically an H1 -receptor-blocking agent belonging to the alkylamine class of antihistamines. Antihistamines appear to compete with histamine for receptor sites on effector cells. Brompheniramine also has anticholinergic (drying) and sedative effects. Among the antihistaminic effects, it antagonizes the allergic response (vasodilation, increased vascular permeability, increased mucus secretion) of nasal tissue. Brompheniramine is well absorbed from the gastrointestinal tract, with peak plasma concentration after single, oral dose of 4 mg reached in 5 hours; urinary excretion is the major route of elimination, mostly as products of biodegradation; the liver is assumed to be the main site of metabolic transformation.

Pseudoephedrine acts on sympathetic nerve endings and also on smooth muscle, making it useful as a nasal decongestant. The nasal decongestant effect is mediated by the action of pseudoephedrine on α-sympathetic receptors, producing vasoconstriction of the dilated nasal arterioles. Following oral administration, effects are noted within 30 minutes with peak activity occurring at approximately one hour.

Dextromethorphan acts centrally to elevate the threshold for coughing. It has no analgesic or addictive properties. The onset of antitussive action occurs in 15 to 30 minutes after administration and is of long duration.

INDICATIONS & USAGE

For relief of coughs and upper respiratory symptoms, including nasal congestion, associated with allergy or the common cold.

CONTRAINDICATIONS

Hypersensitivity to any of the ingredients. Do not use in the newborn, in premature infants, in nursing mothers, or in patients with severe hypertension or severe coronary artery disease. Do not use dextromethorphan in patients receiving monoamine oxidase (MAOI) inhibitors (see PRECAUTIONS - Drug Interactions).
Antihistamines should not be used to treat lower respiratory tract conditions including asthma.

WARNINGS

Especially in infants and small children, antihistamines in overdosage may cause hallucinations, convulsions, and death.
Antihistamines may diminish mental alertness. In the young child, they may produce excitation.

PRECAUTIONS

GENERAL PRECAUTIONS

Because of its antihistamine component, brompheniramine maleate, pseudoephedrine hydrochloride and dextromethorphan hydrobromide syrup should be used with caution in patients with a history of bronchial asthma, narrow angle glaucoma, gastrointestinal obstruction, or urinary bladder neck obstruction. Because of its sympathomimetic component, brompheniramine maleate, pseudoephedrine hydrochloride and dextromethorphan hydrobromide syrup should be used with caution in patients with diabetes, hypertension, heart disease, or thyroid disease.

INFORMATION FOR PATIENTS

Patients should be warned about engaging in activities requiring mental alertness, such as driving a car or operating dangerous machinery.

DRUG INTERACTIONS

Monoamine oxidase (MAO) inhibitors
Hyperpyrexia, hypotension, and death have been reported coincident with the coadministration of MAO inhibitors and products containing dextromethorphan. In addition, MAO inhibitors prolong and intensify the anticholinergic (drying) effects of antihistamines and may enhance the effect of pseudoephedrine. Concomitant administration of brompheniramine maleate, pseudoephedrine hydrochloride and dextromethorphan hydrobromide syrup and MAO inhibitors should be avoided (see CONTRAINDICATIONS).
Central nervous system (CNS) depressants
Antihistamines have additive effects with alcohol and other CNS depressants (hypnotics, sedatives, tranquilizers, antianxiety agents, etc.).
Antihypertensive drugs
Sympathomimetic may reduce the effects of antihypertensive drugs.

CARCINOGENESIS & MUTAGENESIS & IMPAIRMENT OF FERTILITY

Animal studies of brompheniramine maleate, pseudoephedrine hydrochloride and dextromethorphan hydrobromide syrup to assess the carcinogenic and mutagenic potential or the effect on fertility have not been performed.

PREGNANCY

Teratogenic Effects
Pregnancy Category C
Animal reproduction studies have not been conducted with brompheniramine maleate, pseudoephedrine hydrochloride and dextromethorphan hydrobromide syrup. It is also not known whether brompheniramine maleate, pseudoephedrine hydrochloride and dextromethorphan hydrobromide syrup can cause fetal harm when administered to a pregnant woman or can affect reproduction capacity. It should be given to a pregnant woman only if clearly needed.
Reproduction studies of brompheniramine maleate (a component of brompheniramine maleate, pseudoephedrine hydrochloride and dextromethorphan hydrobromide syrup) in rats and mice at doses up to 16 times the maximum human doses have revealed no evidence of impaired fertility or harm to the fetus.

NURSING MOTHERS

Because of the higher risk of intolerance of antihistamines in small infants generally, and in newborns and prematures in particular, brompheniramine maleate, pseudoephedrine hydrochloride and dextromethorphan hydrobromide syrup is contraindicated in nursing mothers.

PEDIATRIC USE

Safety and effectiveness in pediatric patients below the age of 6 months have not been established (see DOSAGE AND ADMINISTRATION).

GERIATRIC USE

Clinical studies of brompheniramine maleate, pseudoephedrine hydrochloride and dextromethorphan hydrobromide syrup did not include sufficient numbers of subjects aged 65 and over to determine whether they respond differently from younger subjects. However, antihistamines are more likely to cause dizziness, sedation, and hypotension in elderly patients. The elderly are also more likely to experience adverse reactions to sympathomimetics.
In general, dose selection for an elderly patient should be cautious, usually starting at the low end of the dosing range, reflecting the greater frequency of decreased hepatic, renal, or cardiac function, and of concomitant disease or other drug therapy.

ADVERSE REACTIONS

The most frequent adverse reactions to brompheniramine maleate, pseudoephedrine hydrochloride and dextromethorphan hydrobromide syrup are: sedation; dryness of mouth, nose and throat; thickening of bronchial secretions; dizziness. Other adverse reactions may include:

Dermatologic: Urticaria, drug rash, photosensitivity, pruritus.

Cardiovascular System: Hypotension, hypertension, cardiac arrhythmias, palpitation.

CNS: Disturbed coordination, tremor, irritability, insomnia, visual disturbances, weakness, nervousness, convulsions, headache, euphoria, and dysphoria.

G.U. System: Urinary frequency, difficult urination.

G.I. System: Epigastric discomfort, anorexia, nausea, vomiting, diarrhea, constipation.

Respiratory System: Tightness of chest and wheezing, shortness of breath.

Hematologic System: Hemolytic anemia, thrombocytopenia, agranulocytosis.

OVERDOSAGE

Signs and Symptoms

Central nervous system effects from overdosage of brompheniramine may vary from depression to stimulation, especially in children. Anticholinergic effects may be noted. Toxic doses of pseudoephedrine may result in CNS stimulation, tachycardia, hypertension, and cardiac arrhythmias; signs of CNS depression may occasionally be seen. Dextromethorphan in toxic doses will cause drowsiness, ataxia, nystagmus, opisthotonos, and convulsive seizures.

Toxic Doses

Data suggest that individuals may respond in an unexpected manner to apparently small amounts of a particular drug. A 2½-year-old child survived the ingestion of 21 mg/kg of dextromethorphan exhibiting only ataxia, drowsiness, and fever, but seizures have been reported in 2 children following the ingestion of 13 to 17 mg/kg. Another 2½-year-old child survived a dose of 300 to 900 mg of brompheniramine. The toxic dose of pseudoephedrine should be less than that of ephedrine, which is estimated to be 50 mg/kg.

Treatment

Induce emesis if patient is alert and is seen prior to 6 hours following ingestion. Precautions against aspiration must be taken, especially in infants and small children. Gastric lavage may be carried out, although in some instances tracheostomy may be necessary prior to lavage. Naloxone hydrochloride 0.005 mg/kg intravenously may be of value in reversing the CNS depression that may occur from an overdose of dextromethorphan. CNS stimulants may counter CNS depression. Should CNS hyperactivity or convulsive seizures occur, intravenous short-acting barbiturates may be indicated. Hypertensive responses and/or tachycardia should be treated appropriately. Oxygen, intravenous fluids, and other supportive measures should be employed as indicated.

DOSAGE & ADMINISTRATION

Adults and pediatric patients 12 years of age and over: 10 mL (2 teaspoonfuls) every 4 hours. Children 6 to under 12 years of age: 5 mL (1 teaspoonful) every 4 hours. Children 2 to under 6 years of age: 2.5 mL (½ teaspoonful) every 4 hours. Infants 6 months to under 2 years of age: Dosage to be established by a physician.
Do not exceed 6 doses during a 24-hour period.

HOW SUPPLIED

Brompheniramine maleate, pseudoephedrine hydrochloride and dextromethorphan hydrobromide syrup is a clear, light pink-colored, butterscotch-flavored syrup containing in each 5 mL (1 teaspoonful) brompheniramine maleate 2 mg, pseudoephedrine hydrochloride 30 mg and dextromethorphan hydrobromide 10 mg, available in the following sizes:
4 fl oz (118 mL) NDC 67877-558-17
1 Pint (473 mL) NDC 67877-558-16
RECOMMENDED STORAGE
Store at 20 ° to 25 °C (68 ° to 77 °F) [See USP Controlled Room Temperature].
KEEP TIGHTLY CLOSED
Dispense in a tight, light-resistant container as defined in the USP.
Rx Only

Manufactured by:
Alkem Laboratories Ltd.,
Mumbai - 400 013, INDIA.
Distributed by:
Ascend Laboratories, LLC
Bedminster, NJ 07921

Revised: January, 2025
PT 2859-02

PACKAGE LABEL.PRINCIPAL DISPLAY PANEL

NDC 67877-558-17
Brompheniramine Maleate, Pseudoephedrine Hydrochloride and Dextromethorphan Hydrobromide Syrup
Each 5 mL (teaspoonful) contains:
Brompheniramine Maleate, USP 2 mg
Pseudoephedrine Hydrochloride, USP 30 mg
Dextromethorphan Hydrobromide, USP 10 mg
Alcohol 0.95% v/v
Rx Only
NET: 4 fl oz (118 mL)
Ascend Laboratories, LLC

NDC 67877-558-16
Brompheniramine Maleate, Pseudoephedrine Hydrochloride and Dextromethorphan Hydrobromide Syrup
Each 5 mL (teaspoonful) contains:
Brompheniramine Maleate, USP 2 mg
Pseudoephedrine Hydrochloride, USP 30 mg
Dextromethorphan Hydrobromide, USP 10 mg
Alcohol 0.95% v/v
Rx Only
NET: 1 Pint (473 mL)
Ascend Laboratories, LLC

Front

Back